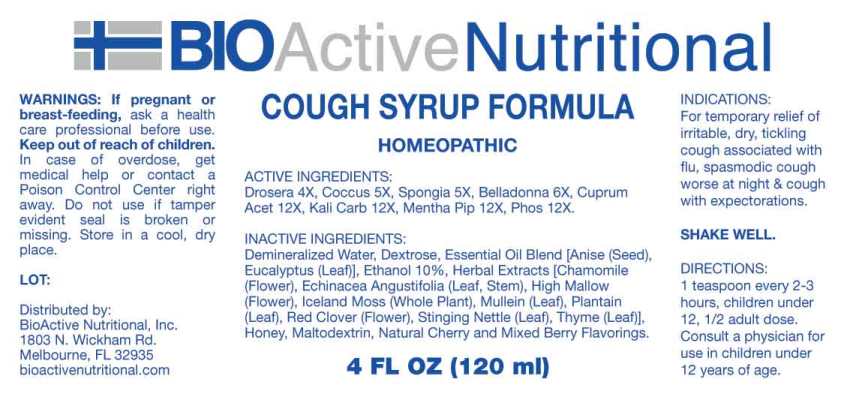 DRUG LABEL: Cough Syrup Formula
NDC: 43857-0548 | Form: LIQUID
Manufacturer: BioActive Nutritional, Inc.
Category: homeopathic | Type: HUMAN OTC DRUG LABEL
Date: 20240105

ACTIVE INGREDIENTS: DROSERA ROTUNDIFOLIA WHOLE 4 [hp_X]/1 mL; PROTORTONIA CACTI 5 [hp_X]/1 mL; SPONGIA OFFICINALIS SKELETON, ROASTED 5 [hp_X]/1 mL; ATROPA BELLADONNA 6 [hp_X]/1 mL; CUPRIC ACETATE 12 [hp_X]/1 mL; POTASSIUM CARBONATE 12 [hp_X]/1 mL; MENTHA X PIPERITA WHOLE 12 [hp_X]/1 mL; PHOSPHORUS 12 [hp_X]/1 mL
INACTIVE INGREDIENTS: CHAMOMILE; ECHINACEA ANGUSTIFOLIA LEAF; MALVA SYLVESTRIS FLOWER; CETRARIA ISLANDICA WHOLE; VERBASCUM THAPSUS LEAF; PLANTAGO MAJOR LEAF; TRIFOLIUM PRATENSE FLOWER; URTICA DIOICA LEAF; THYMUS VULGARIS LEAF; HONEY; WATER; ALCOHOL; CHERRY; BERRY; ANISE OIL; EUCALYPTUS OIL; DEXTROSE, UNSPECIFIED FORM; MALTODEXTRIN

DRUG FACTS:

ACTIVE INGREDIENTS:

Drosera (Rotundifolia) 4X, Coccus Cacti 5X, Spongia Tosta 5X, Belladonna 6X, Cuprum Aceticum 12X, Kali Carbonicum 12X, Mentha Piperita 12X, Phosphorus 12X.

INDICATIONS:

For temporary relief of irritable, dry, tickling cough associated with flu, spasmodic cough worse at night & cough with expectorations.

WARNINGS:

If pregnant or breast-feeding, ask a health care professional before use.

Keep out of reach of children. In case of overdose, get medical help or contact a Poison Control Center right away.

Do not use if tamper evident seal is broken or missing.

Store in cool, dry place.

KEEP OUT OF REACH OF CHILDREN:

In case of overdose, get medical help or contact a Poison Control Center right away.

DIRECTIONS:

SHAKE WELL.

1 teaspoon every 2-3 hours, children under 12, 1/2 adult dose.

Consult a physician for use in children under 12 years of age.

INDICATIONS:

For temporary relief of irritable, dry, tickling cough associated with flu, spasmodic cough worse at night & cough with expectorations.

INACTIVE INGREDIENTS:

Demineralized Water, Dextrose, Essential Oil Blend [Anise (Seed), Eucalyptus (Leaf)], Ethanol, 10% Herbal Extracts [Chamomile (Flower), Echinacea Angustifolia (leaf, stem), High Mallow (Flower), Iceland Moss (Whole Plant), Mullein (Leaf), Plantain (Leaf), Red Clover (Flower), Stinging Nettle (Leaf), Thyme (Leaf)], Honey, Natural Cherry Flavor, Natural Mixed Berry Flavor.

QUESTIONS:

Distributed by:

BioActive Nutritional, Inc.

1803 N. Wickham Rd.

Melbourne, FL 32935

bioactivenutritional.com

PACKAGE LABEL DISPLAY:

BioActive Homeopathic

COUGH SYRUP FORMULA

4 FL OZ (120 ml)